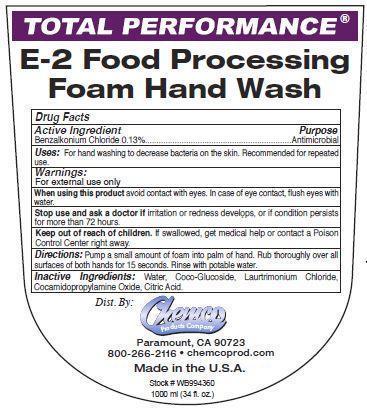 DRUG LABEL: E-2 Food Processing Foam Hand Wash
NDC: 63039-1002 | Form: LIQUID
Manufacturer: Chemco Products Company
Category: otc | Type: HUMAN OTC DRUG LABEL
Date: 20241125

ACTIVE INGREDIENTS: BENZALKONIUM CHLORIDE 1.3 mg/1 mL
INACTIVE INGREDIENTS: WATER; COCO GLUCOSIDE; LAURTRIMONIUM CHLORIDE; COCAMIDOPROPYLAMINE OXIDE; CITRIC ACID MONOHYDRATE

Drug Facts 63039-1002

Active Ingredient

Benzalkonium Chloride 0.13%

Purpose

Antimicrobial

Uses:

For hand washing to decrease bacteria on the skin.

Recommended for repeated use.

Warnings:

For external use only

When using this product avoid contact with eyes.

In case of eye contact, flush eyes with water.

Stop use and ask a doctor if irritation or redness develops, or if condition persists for more than 72 hours.

Keep out of reach of children.

If swallowed, get medical help or contact a Poison Control Center right away.

Directions:

Pump a small amount of foam into palm of hand.

Rub thoroughly over all surfaces of both hands for 15 seconds.

Rinse with potable water.

Inactive Ingredients:

Water, Coco-Glucoside, Laurtrimonium Chloride, Cocamidopropylamine Oxide, Citric Acid.

PACKAGE LABEL

Total Performance

E-2 Food Processsing

Foam Hand Wash

Dist. By:

Chemco

Products Company

Paramount, CA 90723

800-266-2116 chemcoprod.com

Made in the U.S.A.

Stock # WB994360

1000 ml (34 fl. oz.)